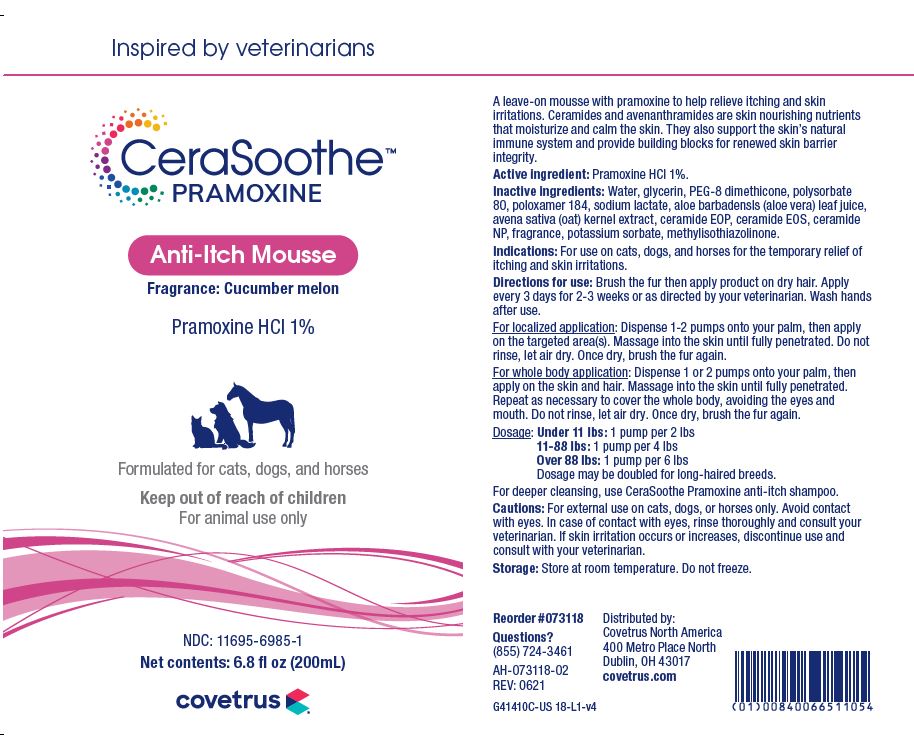 DRUG LABEL: CeraSoothe
NDC: 11695-6985 | Form: LIQUID
Manufacturer: Butler Animal Health Supply, LLC dba Covetrus North America
Category: animal | Type: OTC ANIMAL DRUG LABEL
Date: 20220526

ACTIVE INGREDIENTS: PRAMOXINE HYDROCHLORIDE 10 mg/1 mL
INACTIVE INGREDIENTS: WATER; GLYCERIN; PEG-8 DIMETHICONE; POLYSORBATE 80; POLOXAMER 184; ALOE VERA LEAF; AVENANTHRAMIDES; CERAMIDE 1; CERAMIDE EOS; CERAMIDE NP; POTASSIUM SORBATE; METHYLISOTHIAZOLINONE

DESCRIPTION

CeraSoothe PRAMOXINE

Anti-itch Mousse

Fragrance: Cucumber melon

Formulated for cats, dogs, and horses

A leave-on mousse with pramoxine to help relieve itching and skin irritations. Ceramides and avenanthramides are skin nourishing nutriients that moisturize and calm the skin. The also support the skin's natural immune system and provide building blocks for renewed skin barrier integrity.

Active ingredients: Pramoxine HCl 1%.

Inactive ingredients: Water, glycerin, PEG-8 dimethicone, polysorbate 80, poloxamer 184, sodium lactate, aloe barbadensis (aloe) leaf juice, avena sativa (oat) kernel extract, ceramide EOP, ceramide EOS, ceramide NP, fragrance, potassium sorbate, methylisothiazolinone.

INDICATIONS AND USAGE

Indications: For use on cats, dogs and horses for the temporary relief of itching and skin irritations.

Directions for use: Brush the fur then apply product on dry hair. Apply every 3 days for 2-3 weeks or as directed by your veterinarian. Wash hands after use.

For localized application: Dispense 1 - 2 pumps onto your palm, then apply on the targeted area(s). Massage into the skin until fully penetrated. Do not rinse, let air dry. Once dry, brush the fur again.

For whole body application: Dispense 1 or 2 pumps onto your palm, then apply on the skin and hair. Massage into the skin until fully penetrated. Repeat as necessary to cover the whole body, avoiding the eyes and mouth. Do not rinse, let air dry. Once dry, brush the fur again.

Dosage:

Under 11 lbs: 1 pump per 2 lbs

11-88 lbs: 1 pump per 4 lbs

Over 88 lbs: 1 pump per 6 lbs

Dosage may be doubled for long-haired dogs.

For deeper cleansing, use Ceraven Pramoxine anti-itch shampoo.

WARNINGS AND PRECAUTIONS

Cautions: For external use on cats, dogs or horses only. Avoid contact with eyes. In case of contact with eyes, rinse thoroughly and consult your veterinarian. If skin irritation occurs or increases, discontinue use and consult with your veterinarian.

Storage: Store at room temperature. Do not freeze.

QUESTIONS?

(855) 724-3461

Distributed by:

Covetrus North America

400 Metro Place North

Dublin, OH 43017

covetrus.com

PRINCIPAL DISPLAY PANEL - 6.8 OUNCE (200 mL) Bottle

Inspired by veteriarians

CeraSoothe PRAMOXINE

Anti-itch Mousse

Fragrance: Cucumber melon

Pramoxine HCl 1%

Formulated for cats, dogs, and horses

Keep out of reach of children

For animal use only

NDC: 11695-6985-1

Net Contents: 6.8 fl oz (200 mL)

covetrus